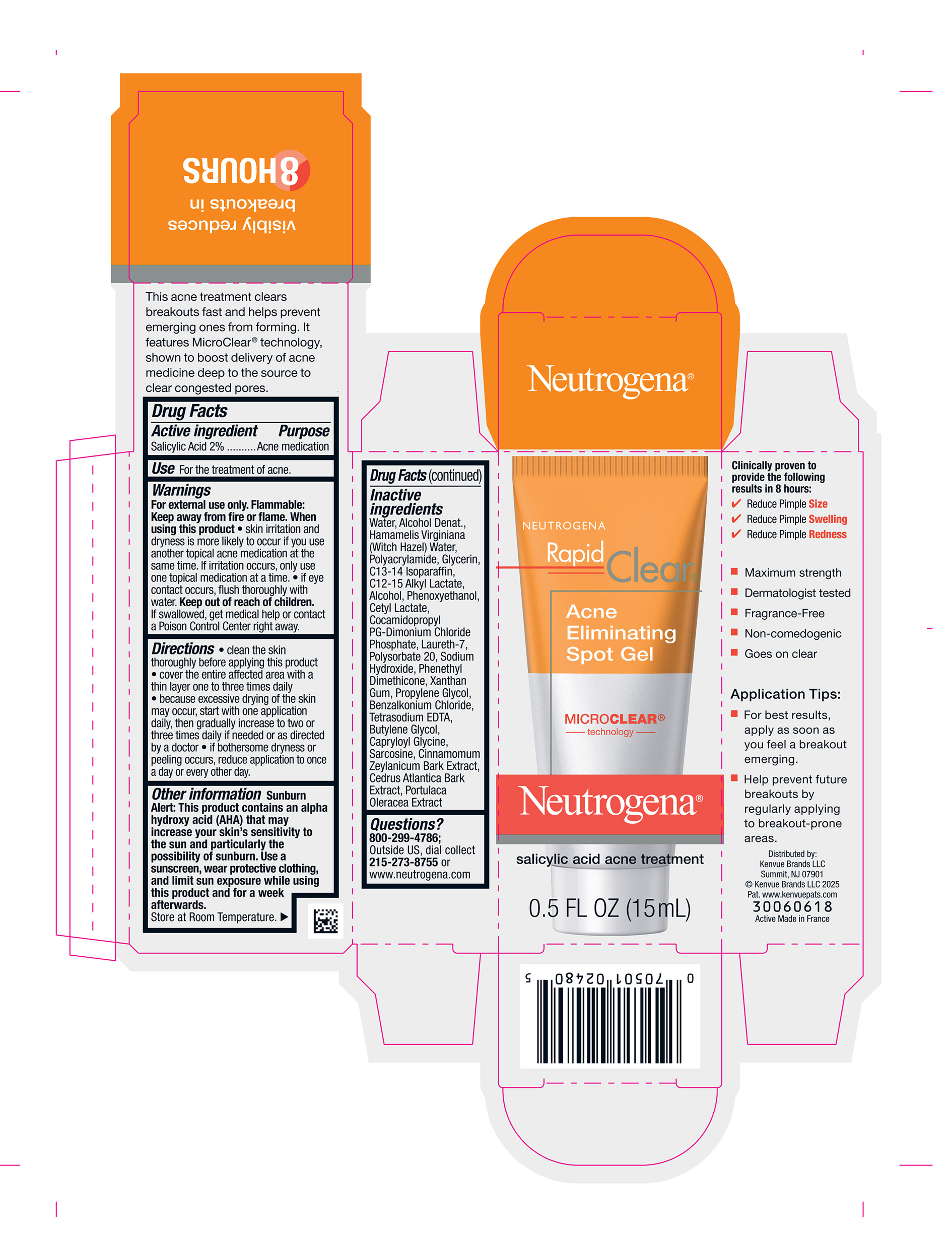 DRUG LABEL: Neutrogena Rapid Clear Acne Eliminating Spot
NDC: 69968-0825 | Form: GEL
Manufacturer: Kenvue Brands LLC
Category: otc | Type: HUMAN OTC DRUG LABEL
Date: 20250707

ACTIVE INGREDIENTS: SALICYLIC ACID 20 mg/1 mL
INACTIVE INGREDIENTS: BUTYLENE GLYCOL; CAPRYLOYL GLYCINE; SARCOSINE; CINNAMON BARK OIL; CEDRUS ATLANTICA BARK; PURSLANE; WATER; HAMAMELIS VIRGINIANA TOP WATER; GLYCERIN; SODIUM HYDROXIDE; C13-14 ISOPARAFFIN; C12-15 ALKYL LACTATE; ALCOHOL; PHENOXYETHANOL; CETYL LACTATE; COCAMIDOPROPYL PROPYLENE GLYCOL-DIMONIUM CHLORIDE PHOSPHATE; LAURETH-7; POLYSORBATE 20; PROPYLENE GLYCOL; BENZALKONIUM CHLORIDE; EDETATE SODIUM; XANTHAN GUM

Neutrogena Rapid Clear Acne Eliminating Spot Gel

Drug Facts

Active ingredient

Salicylic Acid 2%

Purpose

Acne medication

Use

For the treatment of acne.

Warnings

For external use only.

Flammable

Keep away from fire or flame.

When using this product

- skin irritation and dryness is more likely to occur if you use another topical acne medication at the same time. If irritation occurs, only use one topical medication at a time.
- if eye contact occurs, flush thoroughly with water.

Keep out of reach of children. If swallowed, get medical help or contact a Poison Control Center right away.

Directions

- clean the skin thoroughly before applying this product
- cover the entire affected area with a thin layer one to three times daily
- because excessive drying of the skin may occur, start with one application daily, then gradually increase to two or three times daily if needed or as directed by a doctor
- if bothersome dryness or peeling occurs, reduce application to once a day or every other day.

Other information

Sunburn Alert

This product contains an alpha hydroxy acid (AHA) that may increase your skin’s sensitivity to the sun and particularly the possibility of sunburn. Use a sunscreen, wear protective clothing, and limit sun exposure while using this product and for a week afterwards.

Store at Room Temperature.

Inactive ingredients

Water, Alcohol Denat., Hamamelis Virginiana (Witch Hazel) Water, Polyacrylamide, Glycerin, C13-14 Isoparaffin, C12-15 Alkyl Lactate, Alcohol, Phenoxyethanol, Cetyl Lactate, Cocamidopropyl PG-Dimonium Chloride Phosphate, Laureth-7, Polysorbate 20, Sodium Hydroxide, Phenethyl Dimethicone, Xanthan Gum, Propylene Glycol, Benzalkonium Chloride, Tetrasodium EDTA, Butylene Glycol, Capryloyl Glycine, Sarcosine, Cinnamomum Zeylanicum Bark Extract, Cedrus Atlantica Bark Extract, Portulaca Oleracea Extract

Questions?

800-299-4786; Outside US, dial collect 215-273-8755 or www.neutrogena.com

Distributed by:

Kenvue Brands LLC
Summit, NJ 07901

PRINCIPAL DISPLAY PANEL - 15 mL Tube Carton

NEUTROGENA

Rapid

Clear®

Acne

Eliminating

Spot Gel

MICRO CLEAR®

technology

Neutrogena®

salicylic acid acne treatment

0.5 FL OZ (15mL)